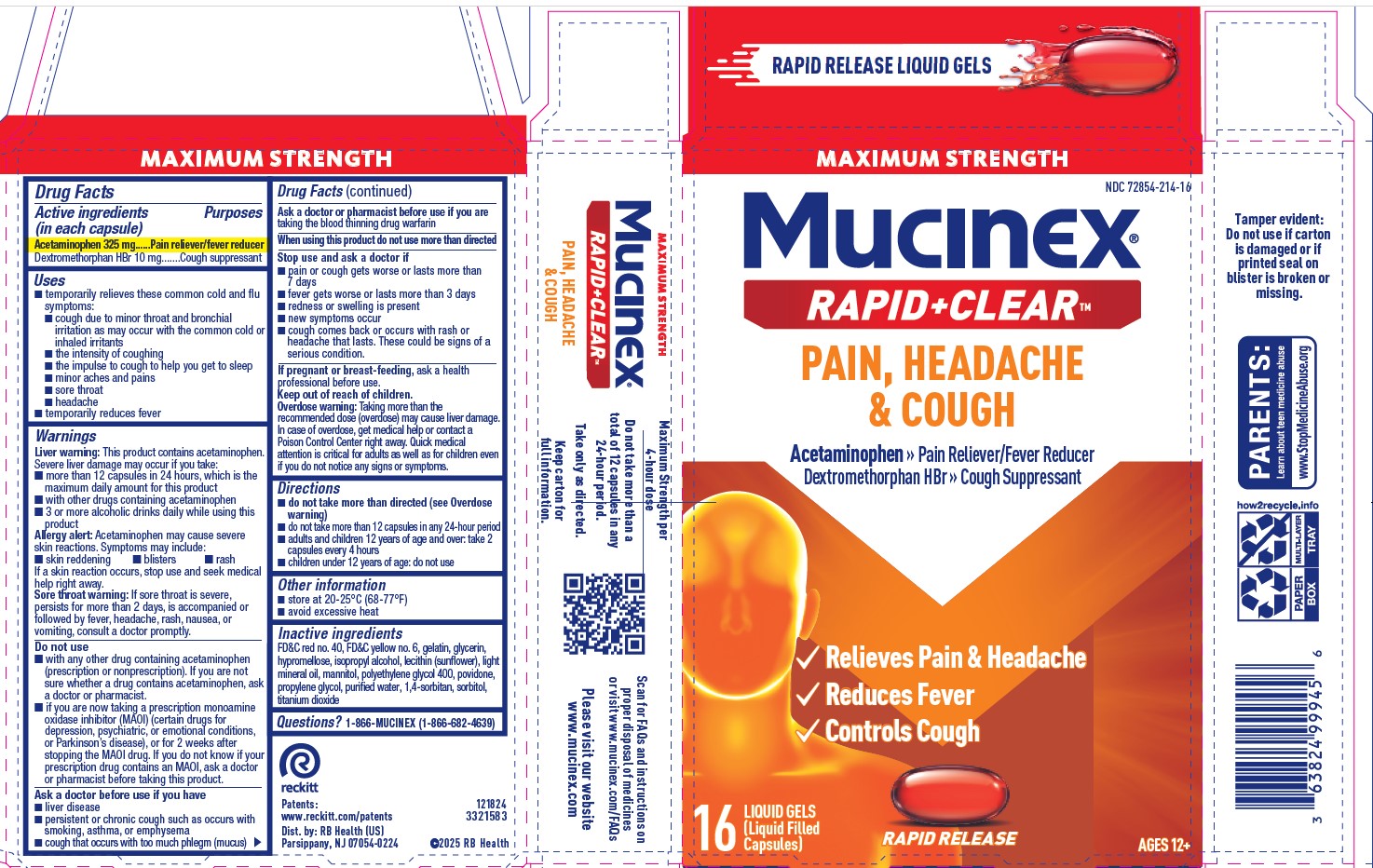 DRUG LABEL: Mucinex Rapid Clear Daytime Pain, Headache, and Cough
NDC: 72854-214 | Form: CAPSULE, LIQUID FILLED
Manufacturer: RB Health (US) LLC
Category: otc | Type: HUMAN OTC DRUG LABEL
Date: 20250618

ACTIVE INGREDIENTS: ACETAMINOPHEN 325 mg/1 1; DEXTROMETHORPHAN HYDROBROMIDE 10 mg/1 1
INACTIVE INGREDIENTS: SORBITOL; FD&C YELLOW NO. 6; GELATIN, UNSPECIFIED; GLYCERIN; HYPROMELLOSE, UNSPECIFIED; ISOPROPYL ALCOHOL; LIGHT MINERAL OIL; POLYETHYLENE GLYCOL, UNSPECIFIED; WATER; POVIDONE, UNSPECIFIED; PROPYLENE GLYCOL; TITANIUM DIOXIDE; 1,4-SORBITAN; LECITHIN, SUNFLOWER; MANNITOL

MUCINEX® Rapid Clear® Liquid Gels Pain, Headache & Cough

Drug Facts

Active ingredients (in each liquid gel) Purposes
Acetaminophen 325 mg Pain reliever/fever reducer
Dextromethorphan HBr 10 mg Cough suppressant

PURPOSE

Active ingredients (in each liquid gel) | Purposes
Acetaminophen 325 mg | Pain reliever/fever reducer
Dextromethorphan HBr 10 mg | Cough suppressant

Uses

temporarily relieves these common cold and flu symptoms:

■ cough due to minor throat and bronchial irritation as
may occur with the common cold or inhaled irritants
■ the intensity of coughing
■ the impulse to cough to help you get to sleep
■ minor aches and pains
■ sore throat
■ headache
■ temporarily reduces fever

Warnings

This product contains acetaminophen. Severe liver damage may occur if you take:

more than 12 liquid gels in 24 hours, which is the maximum daily amount
with other drugs containing acetaminophen
3 or more alcoholic drinks daily while using this product

Liver warning

This product contains acetaminophen. Severe liver damage may occur if you take:

- more than 12 liquid gels in 24 hours, which is the maximum daily amount
- with other drugs containing acetaminophen
- 3 or more alcoholic drinks daily while using this product

Allergy alert

Acetaminophen may cause severe skin reactions. Symptoms may include:

- skin reddening
- blisters
- rash

If a skin reaction occurs, stop use and seek medical help right away.

Sore throat warning

If sore throat is severe, persists for more than 2 days, is accompanied or followed by fever, headache, rash, nausea, or vomiting, consult a doctor promptly.

Do not use

- with any other drug containing acetaminophen (precription or nonprescription). If you are not sure whether a drug contains acetaminophen, ask a doctor or pharmacist.
- if you are now taking a precription monoamine oxidase inhibitor (MAOI) (certain drugs for depression, psychiatric, or emotional conditions, or Parkinson's disease), or for 2 weeks after stopping the MAOI drug. If you do not know if your precription drug contains an MAOI, ask a doctor or pharmacist before taking this product.

Ask a doctor before use if you have

- liver disease
- heart disease
- diabetes
- high blood pressure
- thyroid disease
- trouble urinating due to an enlarged prostate gland
- persistant or chronic cough such as occurs with smoking, asthma, chronic bronchitis, or emphysema
- cough that occurs with too much phlegm (mucus)

Ask a doctor or pharmacist before use if you are taking the blood thinning drug warfarin

When using this product do not use more than directed

Stop use and ask a doctor if

■ pain or cough gets worse or lasts more than 7 days
■ fever gets worse or lasts more than 3 days
■ redness or swelling is present
■ new symptoms occur
■ cough comes back or occurs with rash or headache that
lasts. These could be signs of a serious condition.

PREGNANCY OR BREAST FEEDING

If pregnant or breast-feeding, ask a health professional before use.

Keep out of reach of children.

Overdose warning

Taking more than the recommended dose (overdose) may cause liver damage. In case of overdose, get medical help or contact a Poison Control Center right away. Quick medical attention is critical for adults as well as for children even if you do not notice any signs or symptoms.

Directions

- do not take more than directed (see Overdose warning)
- do not take more than 12 liquid gels in any 24-hour period
- adults and children 12 years of age and over: take 2 liquid gels every 4 hours
- children under 12 years of age: do not use

Other information

- store at 20-25°C (68-77°F)
- avoid excessive heat

Inactive ingredients

FD&C red no. 40, FD&C yellow
no. 6, gelatin, glycerin, hypromellose, isopropyl alcohol,
lecithin (sunflower), light mineral oil, mannitol, polyethylene
glycol 400, povidone, propylene glycol, purified water,
1,4-sorbitan, sorbitol, titanium dioxide

Questions?

1-866-MUCINEX (1-866-682-4639)

You may also report side effects to this phone number.

Dist. by: RB Health (US)
Parsippany, NJ 07054-0224

PRINCIPAL DISPLAY PANEL - 16 Capsule Blister Pack Carton

Fast Dissolving Liquid Gels!

NDC 72854-214

MAXIMUM STRENGTH

MUCINEX®

Acetaminophen – Pain Reliever/Fever Reducer
Dextromethorphan HBr – Cough Suppressant

LIQUID GELS
(Liquid Filled Capsules)

Actual Size

FOR AGES 12 +